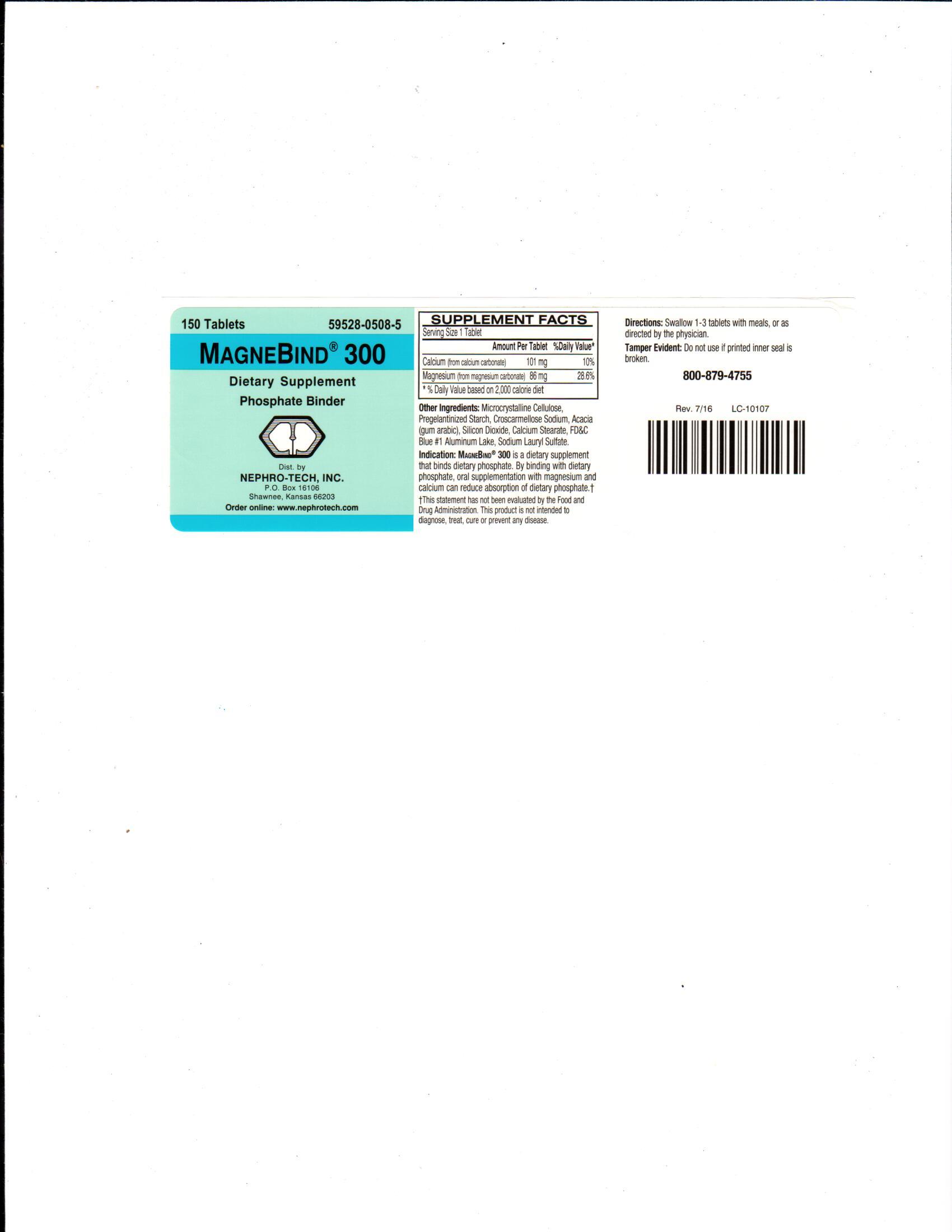 DRUG LABEL: MagneBind 300
NDC: 59528-0508 | Form: TABLET, FILM COATED
Manufacturer: Nephro-Tech, Inc.
Category: other | Type: DIETARY SUPPLEMENT
Date: 20210716

ACTIVE INGREDIENTS: MAGNESIUM CARBONATE 300 mg/1 1; CALCIUM CARBONATE 250 mg/1 1

MagneBind 300 (magnesium carbonate and calcium carbonate)

Principal Display Panel

150 Tablets

59528-0508-5

MagneBind 300

Dietary Supplement

Phosphate Binder

Directions

Swallow 1-3 tablets with meals, or as directed by the physician.

Dietary Supplement Phosphate Binder

MagneBind 300 is a dietary supplement that binds dietary phosphate. By binding with dietary phosphate, oral supplementation with magnesium and calcium can reduce absorption of dietary phosphate. †

†This statement has not been evaluated by the Food and Drug Administration. This product is not intended to diagnose, treat, cure or prevent any disease.